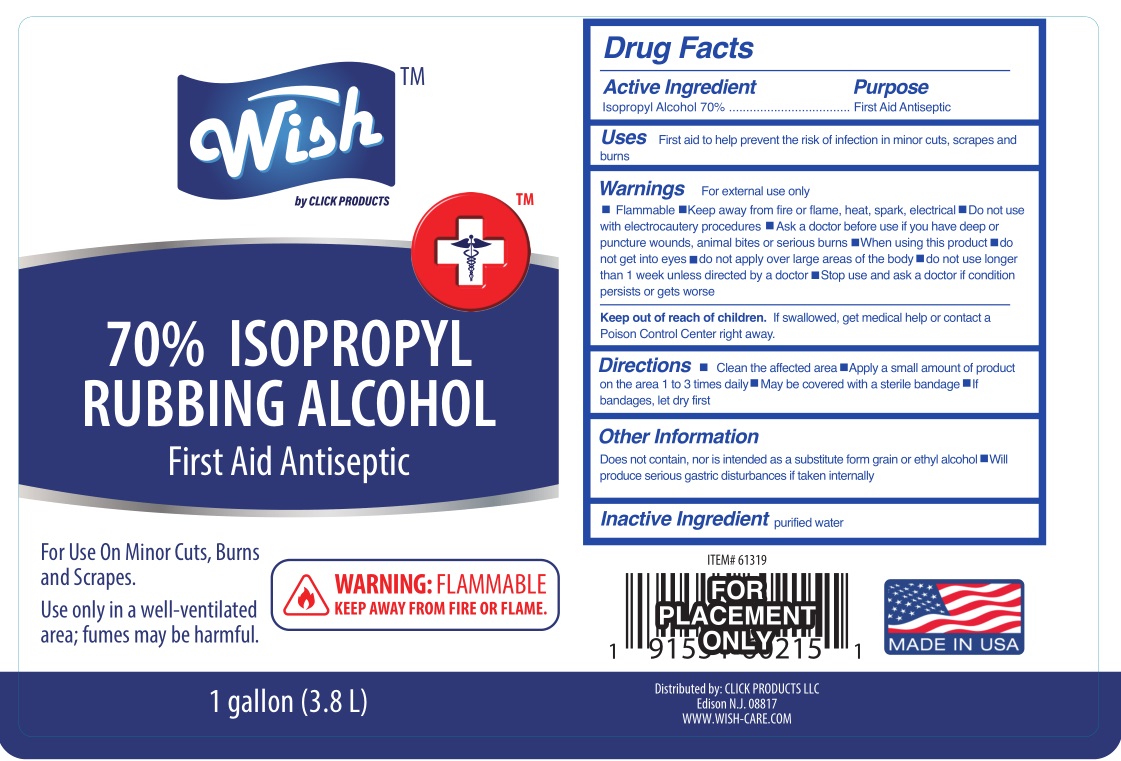 DRUG LABEL: Wish 70% Isopropyl Rubbing Alcohol
NDC: 71611-476 | Form: LIQUID
Manufacturer: Click Products LLC
Category: otc | Type: HUMAN OTC DRUG LABEL
Date: 20200818

ACTIVE INGREDIENTS: ISOPROPYL ALCOHOL 0.7 mL/1 mL
INACTIVE INGREDIENTS: WATER

Wish 70% isopropyl rubbing alcohol

Active ingredient (by volume)

Isopropyl alcohol (70% concentrate)

Purpose

Topical antimicrobial

Uses

- to decrease germs in minor cuts and scrapes
- helps relieve minor muscular aches due to exertion

Warnings

For external use only

- flammable, keep away from fire and flame
- will produce serious gastric disturbances if taken internally

Ask a doctor before use if you have

deep puncture wounds or serious burns

When using this product

- do not get into eyes or mucous membranes
- use only in a well-ventilated area

Stop use and ask a doctor if condition persists or gets worse

condition persists or gets worse

Keep out of reach of children.

In case of an accidental ingestion, contact a Poison Control Center immediately

Directions

- apply to skin directly of with clean gauze, cotton or swab
- for rubbing apply liberally and rub with hands

Other information

- does not contain, nor is intended as a substitute for grain or ethyl alcohol
- keep bottle tightly closed

Inactive ingredient

Water

PACKAGE LABEL

3785 mL NDC: 71611-476-28